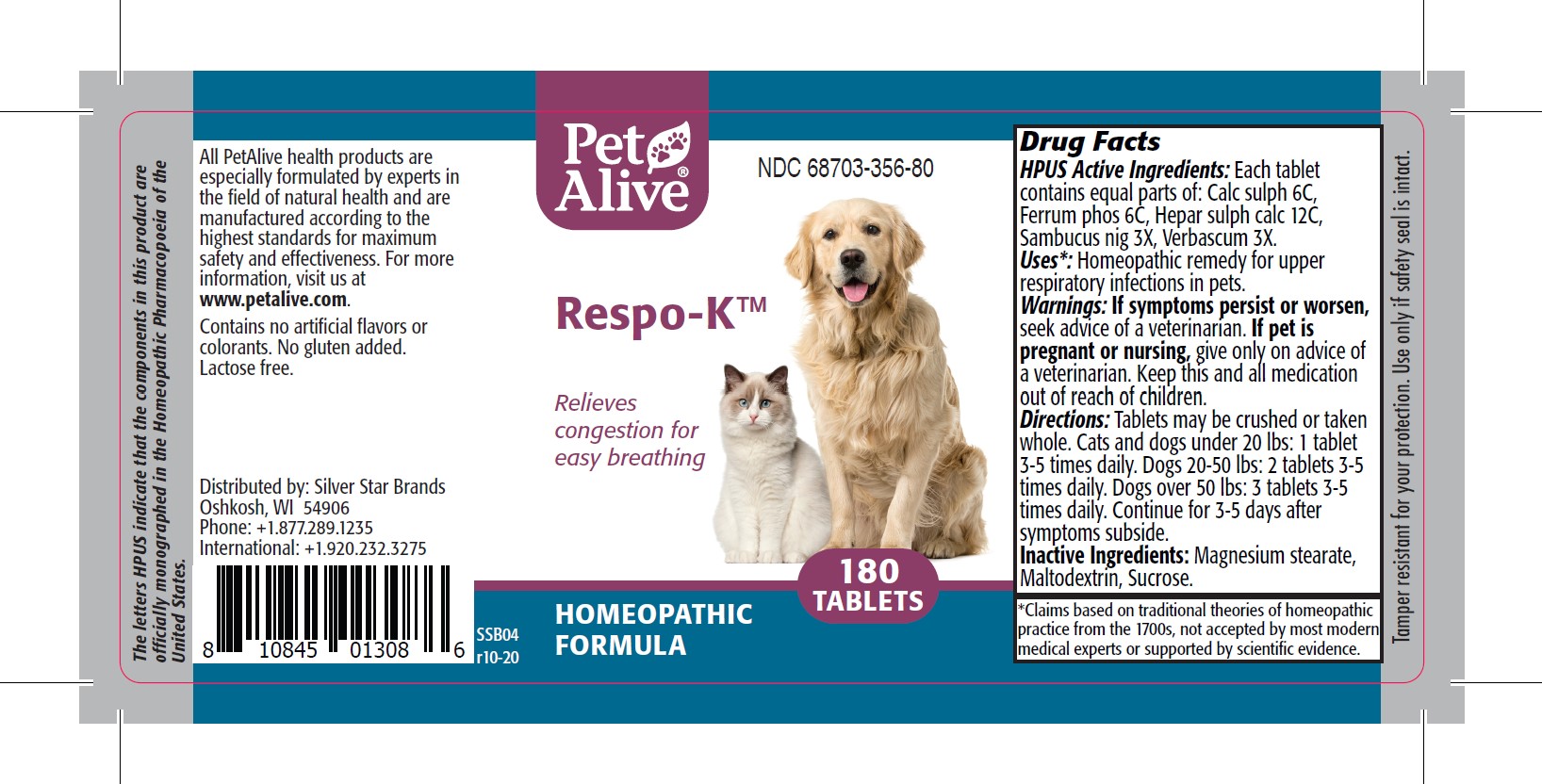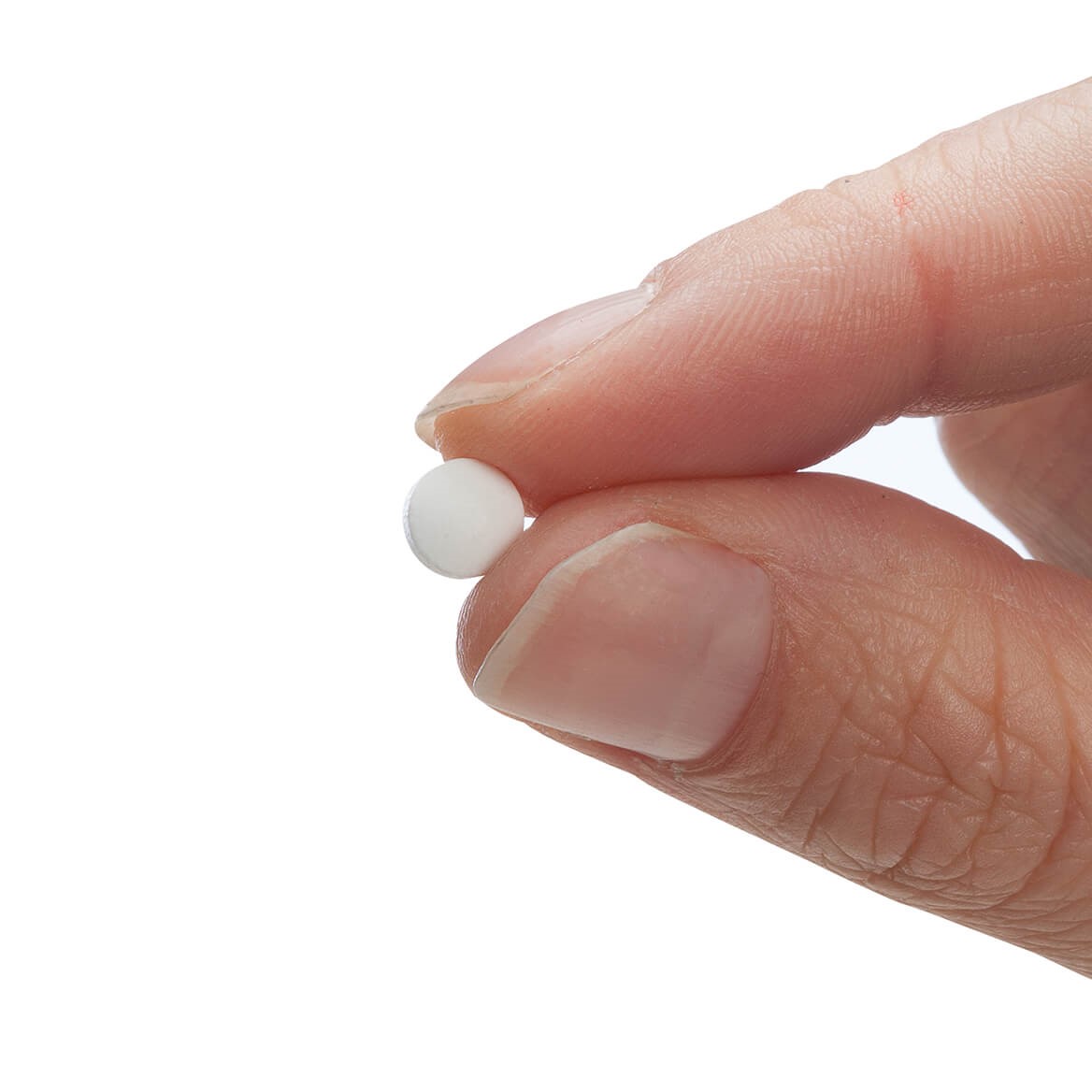 DRUG LABEL: Respo-K
NDC: 68703-356 | Form: TABLET
Manufacturer: SILVER STAR BRANDS
Category: homeopathic | Type: HUMAN OTC DRUG LABEL
Date: 20251212

ACTIVE INGREDIENTS: CALCIUM SULFATE 6 [hp_C]/180 1; FERROSOFERRIC PHOSPHATE 6 [hp_C]/180 1; CALCIUM SULFIDE 12 [hp_C]/180 1; VERBASCUM THAPSUS 3 [hp_X]/180 1; EUROPEAN ELDERBERRY 3 [hp_X]/180 1
INACTIVE INGREDIENTS: MAGNESIUM STEARATE; MALTODEXTRIN; SUCROSE

PetAlive® Respo-K™ Tablets

HPUS Active Ingredients: Each tabelt contains equal parts of: Calc sulph 6C, Ferrum phos 6C, Hepar sulph calc 12C, Sambucus nig 3X, Verbascum 3X.

Uses*

Uses*: Homeopathic remedy for upper respiratory infections in pets.

Warnings

Warnings: If symptoms persist or worsen, seek advice of a veterinarian. If pet is pregnant or nursing, give only on advice of a veterinarian. Keep this and all medication out of reach of children.

Directions

Directions: Tablets may be crushed or taken whole. Cats and dogs under 20lbs: 1 tablet 3-5 times daily. Dogs 20-50lbs: 2 tablets 3-5 times daily. Dogs over 50 lbs: 3 tablets 3-5 times daily. Continue for 3-5 days after symptoms subside.

OTHER SAFETY INFORMATION

Tamper resistant for your protection. Use only if safety seal is intact.

Contains no artificial flavors or colorants. No gluten added. Lactose free.

Inactive ingredients

Inactive ingredients: Magnesium stearate, Maltodexxtrin, Sucrose.

KEEP OUT OF REACH OF CHILDREN

Keep this and all medication out of reach of children.

PURPOSE

Relieves congestion for easy breathing